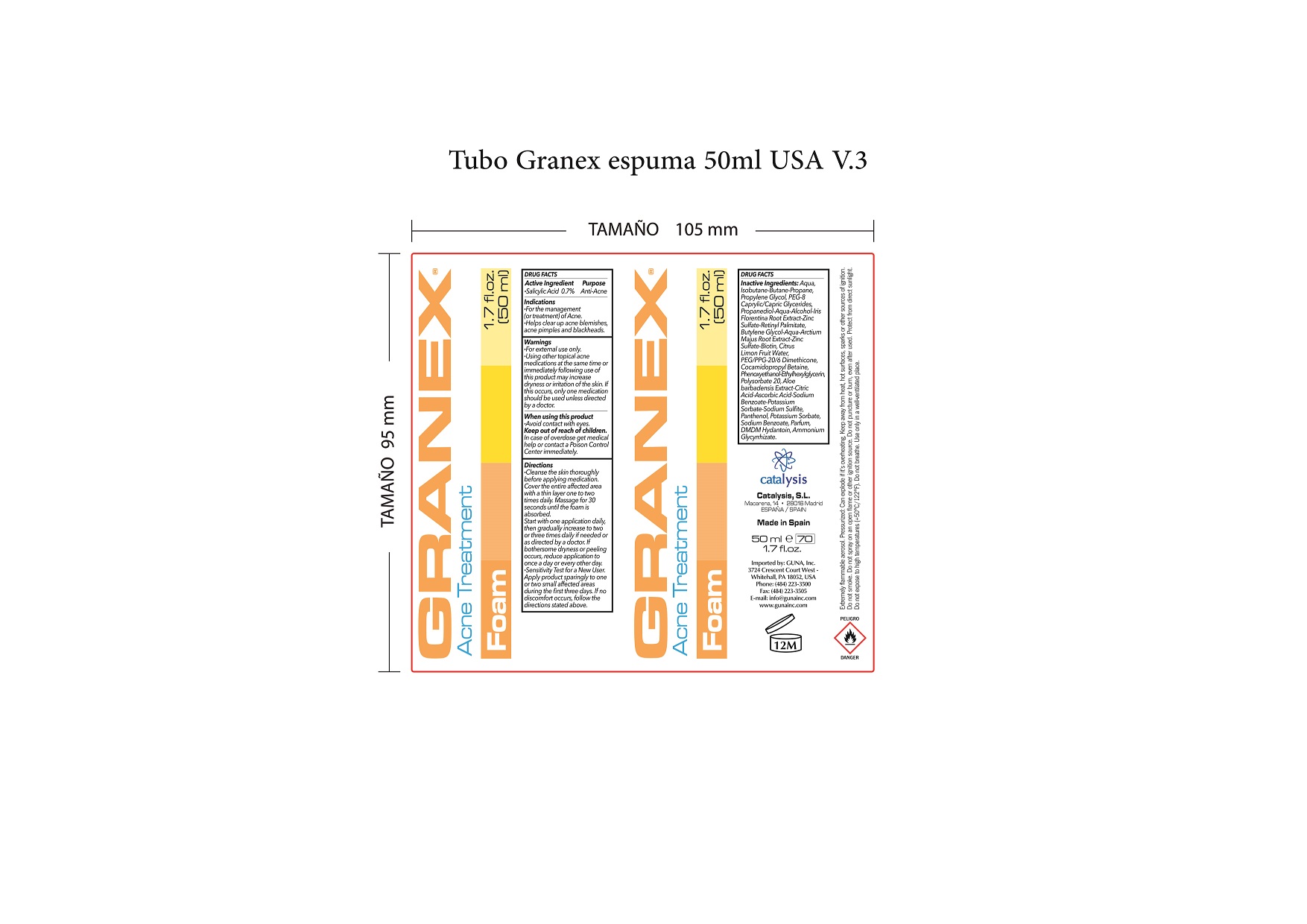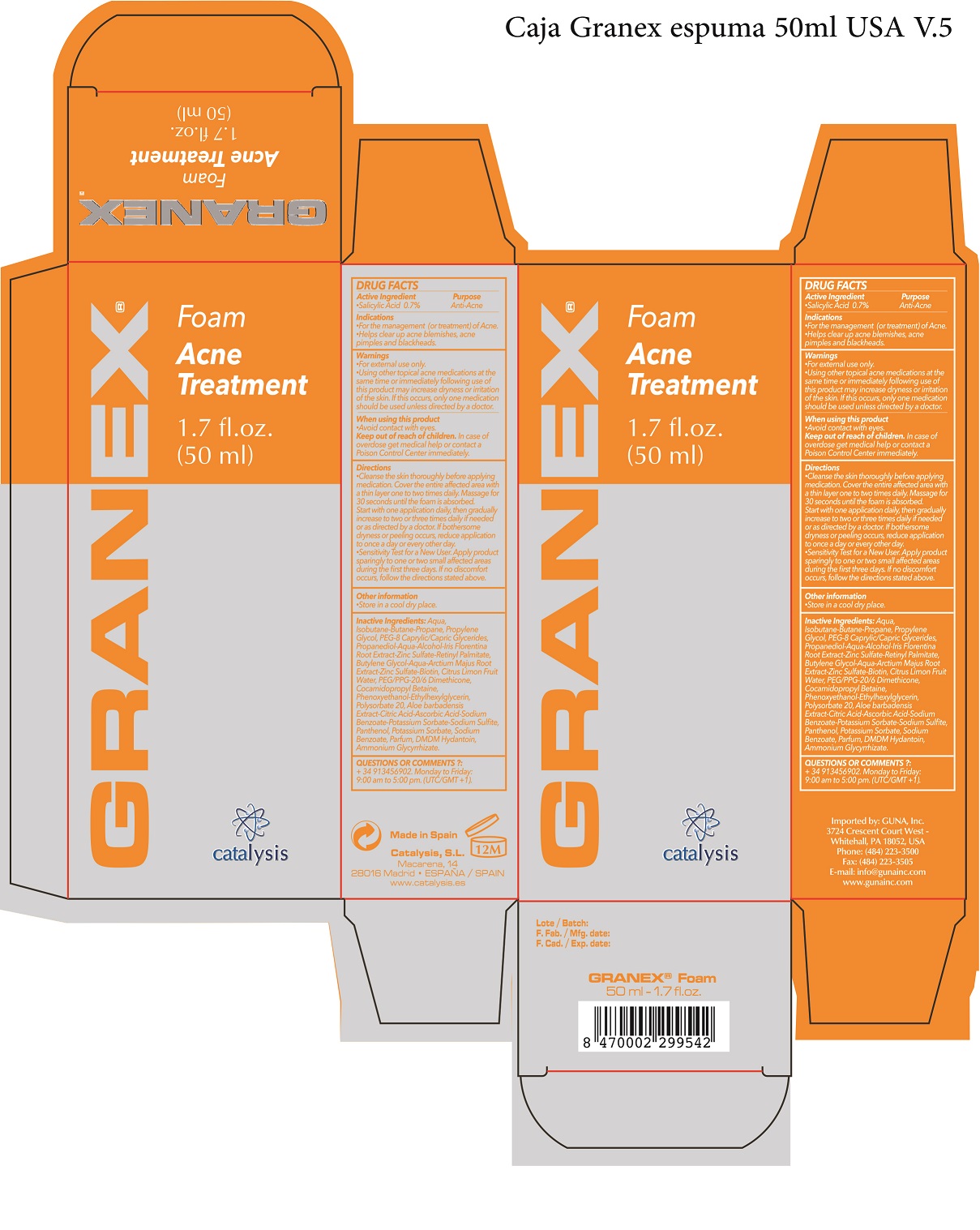 DRUG LABEL: Granex Foam Acne Treatment
NDC: 64539-008 | Form: AEROSOL, FOAM
Manufacturer: Catalysis, SL
Category: otc | Type: HUMAN OTC DRUG LABEL
Date: 20180113

ACTIVE INGREDIENTS: SALICYLIC ACID 0.7 mg/1 mL
INACTIVE INGREDIENTS: BUTYLENE GLYCOL 2.25 mg/1 mL; BIOTIN 2.25 mg/1 mL; PEG/PPG-20/6 DIMETHICONE 1.8 mg/1 mL; PHENOXYETHANOL 0.9 mg/1 mL; ETHYLHEXYLGLYCERIN 0.9 mg/1 mL; ALOE 0.45 mg/1 mL; CITRIC ACID MONOHYDRATE 0.45 mg/1 mL; ASCORBIC ACID 0.45 mg/1 mL; PANTHENOL 0.45 mg/1 mL; GLYCYRRHIZIN 0.09 mg/1 mL; COCAMIDOPROPYL BETAINE 1.35 mg/1 mL; ISOBUTANE 6 mg/1 mL; POTASSIUM SORBATE 0.45 mg/1 mL; PROPANEDIOL 2.25 mg/1 mL; VITAMIN A PALMITATE 2.25 mg/1 mL; ALCOHOL 2.25 mg/1 mL; IRIS X GERMANICA NOTHOVAR. FLORENTINA ROOT 2.25 mg/1 mL; ZINC SULFATE 2.25 mg/1 mL; WATER 2.25 mg/1 mL; ARCTIUM MINUS ROOT 2.25 mg/1 mL; CITRUS X LIMON FRUIT OIL 2.25 mg/1 mL; POLYSORBATE 20 0.54 mg/1 mL; SODIUM BENZOATE 0.45 mg/1 mL; SODIUM SULFITE 0.45 mg/1 mL

Granex Foam Acne Treatment

ACTIVE INGREDIENT

Salicylic Acid 0.7%...............................Anti Acne

- When using this product
- Avoid contact with eyes
- Keep out of reach of children. In case of overdose get medical help or Contact a Poison Control Center right away.

WARNINGS

- For external use only
  - Using other topical acne medications at the same time or immediately following use of this product may increase dryness or irritation of the skin. If this occurs, only one medication should be used unless directed by a doctor

INDICATIONS AND USAGE

- Cleanse the skin thoroughly before applying medication. Cover the entire affected area with a thin layer one to two times daily. Massage for 30 seconds until the foam is absorbed Because excessive drying of the skin may occur. start with one application daily, then gradually increase to two or three times daily if needed or as directed by a doctor. If bothersome dryness or peeling occurs, reduce application to once a day or every other day

- "Sensitivity Test for a New User. Apply product sparingly to one or two small affected areas during the first 3 days. If no discomfort occurs, follow the directions stated above

PURPOSE

For the management (or treatment) of Acne
Helps clear up acne blemishes, acne pimples, blackheads

QUESTIONS

+ 34 913456902 Monday to Friday: 9:00 am to 5:00 pm

OTHER SAFETY INFORMATION

- keep the product in a cool and dry place

DOSAGE AND ADMINISTRATION

- Apply a small amount the intimate parts and gently wash. Rinse with water
- Maybe used as often as necessary

INACTIVE INGREDIENT

Aqua, Isobutane, Butane, Propane, Propylene Glycol, PEG-8 Caprylic/Capric Glycerides, Propanediol, Aqua, Alcohol, Iris Florentina Root Extract, Zinc Sulfate, Retinyl Palmitate, Butylene Glycol, Aqua, Arctium Majus Root Extract, Zinc Sulfate, Biotin, Citrus Limon Fruit Water, PEG/PPG-20/6 Dimethicone, Cocamidopropyl Betaine, Phenoxyethanol, Ethylhexylglycerin, Polysorbate 20, Aloe barbadensis Extract, Citric Acid, Ascorbic Acid, Sodium Benzoate, Potassium Sorbate, Sodium Sulfite , Panthenol, Potassium Sorbate, Sodium Benzoate, Parfum, Glycyrrhizic Acid

PACKAGE LABEL

Granex Foam Anti Acne Treatment